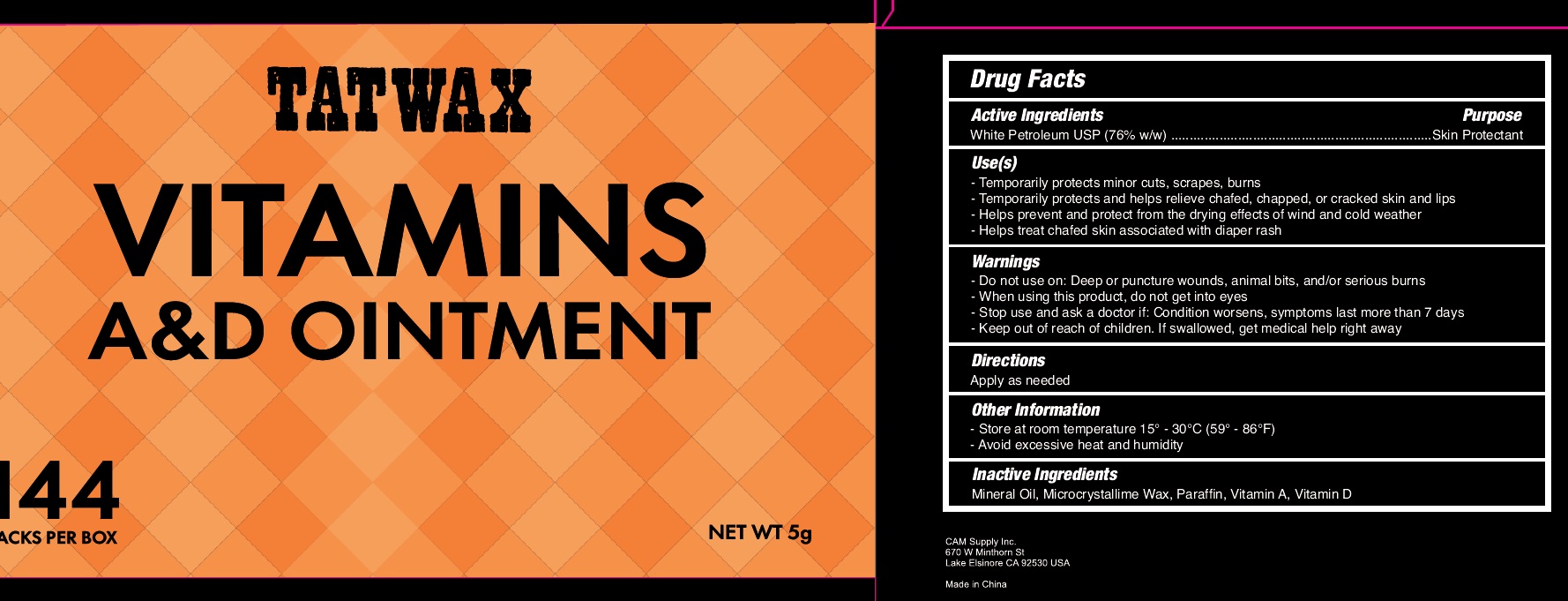 DRUG LABEL: TATWAX VITAMINS AD
NDC: 43473-090 | Form: OINTMENT
Manufacturer: Nantong Health & Beyond Hygienic Products Inc.
Category: otc | Type: HUMAN OTC DRUG LABEL
Date: 20251107

ACTIVE INGREDIENTS: PETROLATUM 76 g/100 g
INACTIVE INGREDIENTS: MINERAL OIL; MICROCRYSTALLINE WAX; PARAFFIN; VITAMIN A; VITAMIN D

43473-090, TALWAX VITAMINS AD Ointment

Active ingredient

White Petroletum, 76% w/w

Purpose

Skin Protectant

Uses

Temporarily protect minor cuts, scrapes, burns

Temporarily protects and helps relieve chafed, chapped, or cracked skin and lips

Helps provent and protect from the drying effects of wind and cold weather

Helps treat chafed skin associated with diaper rash

Warnings

Do not use on: Deep or puncture wounds, animal bites, and/or seruious burns

When using this product, do not get into eyes

Stop useand ask doctor if condition worsens, symptom lasts more than 7 days

Keep out of reach of children. If swallowed, get medical help right away

Directions

Apply as needed

Other information

Store at room temperature 15-30C (59-86F)

Avoid excessive heat and humidity

Inactive ingredients

Mineral Oil, Microcrystalline Wax, Paraffin, Vitamin A, Vitamin D